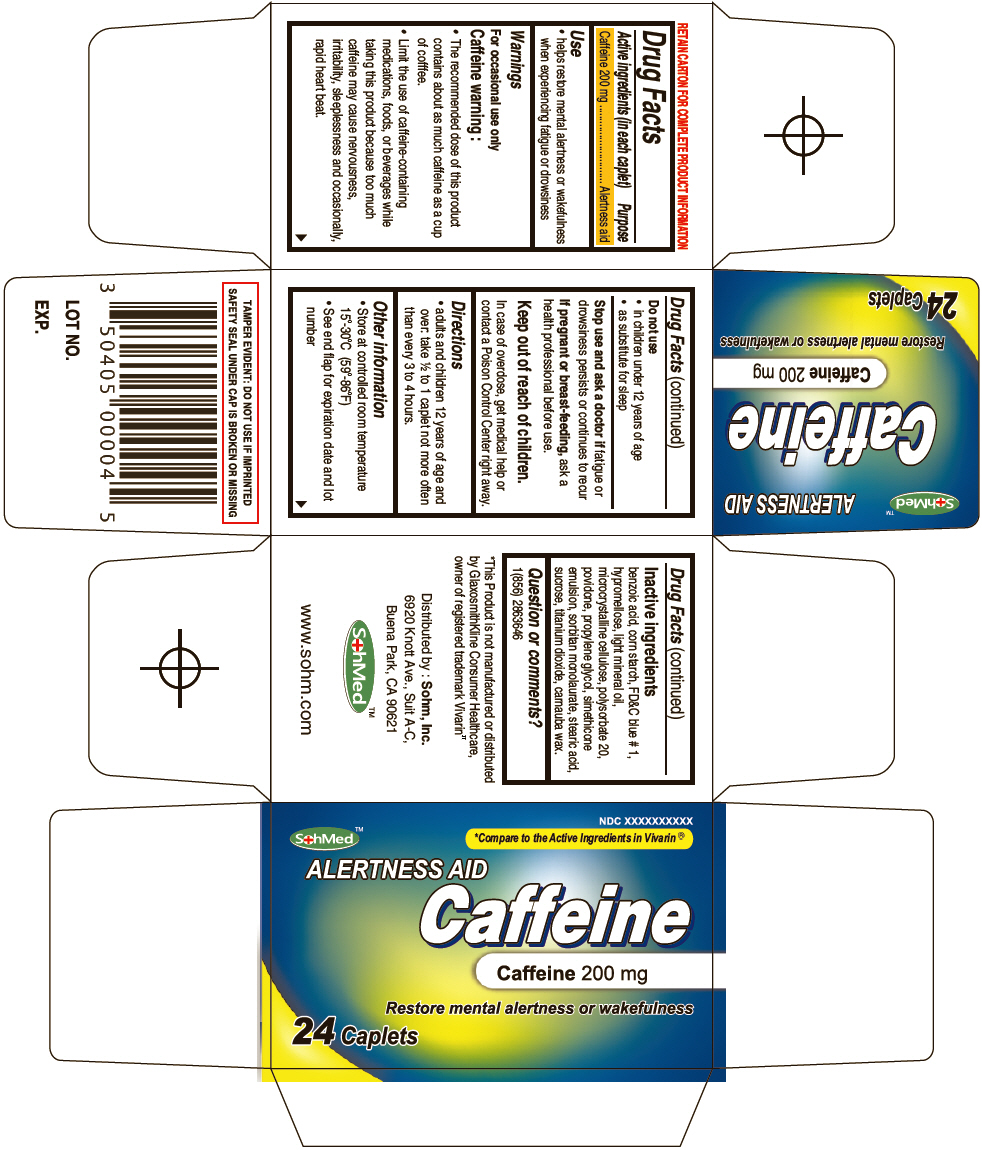 DRUG LABEL: SohMed Alertness Aid
NDC: 50405-005 | Form: TABLET
Manufacturer: SOHM Inc.
Category: otc | Type: HUMAN OTC DRUG LABEL
Date: 20130820

ACTIVE INGREDIENTS: Caffeine 200 mg/1 1
INACTIVE INGREDIENTS: BENZOIC ACID; CARNAUBA WAX; STARCH, CORN; FD&C BLUE NO. 1; HYPROMELLOSES; LIGHT MINERAL OIL; CELLULOSE, MICROCRYSTALLINE; POLYSORBATE 20; POVIDONES; PROPYLENE GLYCOL; DIMETHICONE; SORBITAN MONOLAURATE; STEARIC ACID; SUCROSE; TITANIUM DIOXIDE

SohMed™ Alertness Aid

Drug Facts

Active ingredients (in each caplet)

Caffeine 200 mg

Purpose

Alertness aid

Use

- helps restore mental alertness or wakefulness when experiencing fatigue or drowsiness

Warnings

For occasional use only

Caffeine warning

- The recommended dose of this product contains about as much caffeine as a cup of cofffee.
- Limit the use of caffeine-containing medications, foods, or beverages while taking this product because too much caffeine may cause nervousness, irritability, sleeplessness and occasionally, rapid heart beat.

Do not use

- in children under 12 years of age
- as substitute for sleep

Stop use and ask a doctor if drowsiness persists or continues to recur fatigue or

PREGNANCY OR BREAST FEEDING

If pregnant or breast-feeding, ask a health professional before use.

Keep out of reach of children.

In case of overdose, get medical help or contact a Poison Control Center right away.

Directions

- adults and children 12 years of age and over: take ½ to 1 caplet not more often than every 3 to 4 hours.

Other information

- Store at controlled room temperature 15°-30°C (59°-86°F)
- See end flap for expiration date and lot number

Inactive ingredients

benzoic acid, corn starch, FD&C blue # 1, hypromellose, light mineral oil, microcrystalline cellulose, polysorbate 20, povidone, propylene glycol, simethicone emulsion, sorbitan monolaurate, stearic acid, sucrose, titanium dioxide, carnauba wax.

Question or comments?

1(856) 2863646

Distributed by : Sohm, Inc.
6920 Knott Ave., Suit A-C,
Buena Park, CA 90621

PRINCIPAL DISPLAY PANEL - 24 Caplet Bottle Carton

SohMed™

NDC XXXXXXXXXX

*Compare to the Active Ingredients in Vivarin®

ALERTNESS AID
Caffeine
Caffeine 200 mg

Restore mental alertness or wakefulness

24 Caplets